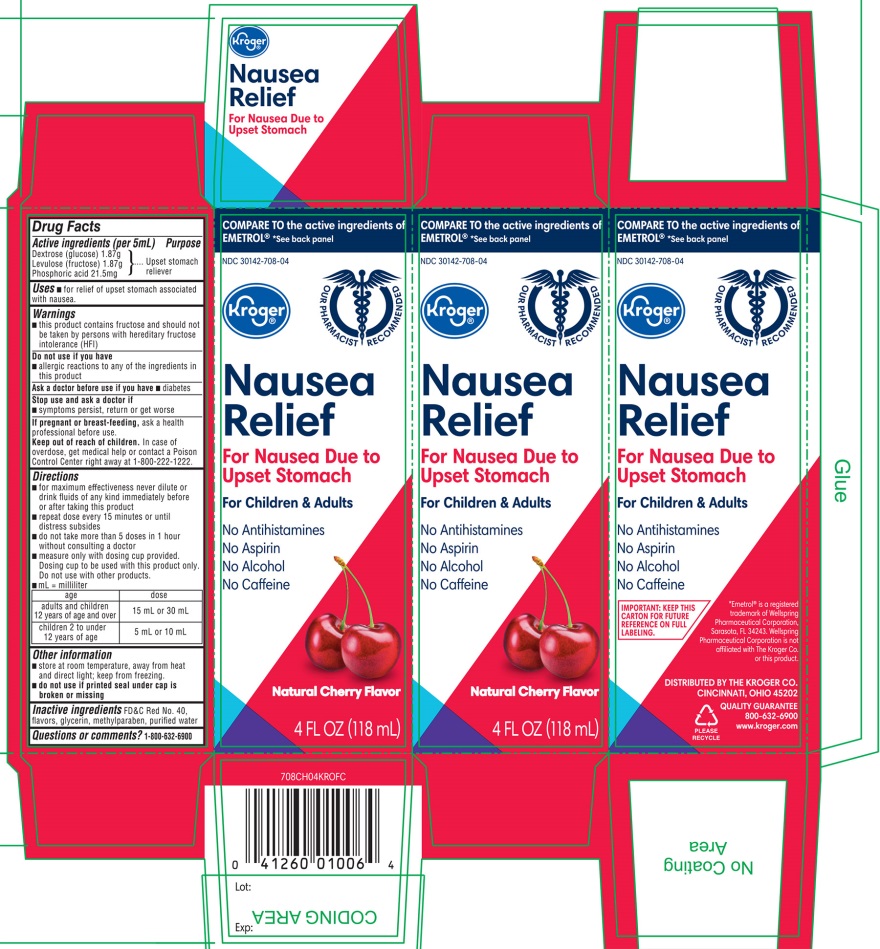 DRUG LABEL: Kroger Anti Nausea

NDC: 30142-708 | Form: LIQUID
Manufacturer: KROGER COMPANY
Category: otc | Type: HUMAN OTC DRUG LABEL
Date: 20250812

ACTIVE INGREDIENTS: DEXTROSE, UNSPECIFIED FORM 1.87 g/5 mL; FRUCTOSE 1.87 g/5 mL; PHOSPHORIC ACID 21.5 mg/5 mL
INACTIVE INGREDIENTS: FD&C RED NO. 40; GLYCERIN; METHYLPARABEN; WATER

Kroger Anti-Nausea Liquid 4FL OZ (118mL) Cherry Flavor

Active ingredients (per 5 mL)

Dextrose (glucose) 1.87 g

Levulose (fructose) 1.87 g

- Phosphoric acid 21.5 mg

Purpose

Upset Stomach Reliever

Uses

- for relief of upset stomach associated with nausea

Warnings

- this product contains fructose and should not be taken by persons with hereditary fructose intolerance (HFI).

Do not use if you have

- allergic reactions to any of the ingredients in this product

Ask a doctor before use if you have

- diabetes

Stop use and ask a doctor if

- symptoms persist, return or get worse

If pregnant or breast-feeding,

ask a health professional before use.

Keep out of reach of children.

In case of overdose, get medical help or contact a Poison Control Center right away at (1-800-222-1222)

Directions

- for maximum effectiveness never dilute or drink fluids of any kind immediately before or after taking this product
- repeat dose every 15 minutes or until distress subsides
- do not take more than 5 doses in 1 hour without consulting a doctor
- measure only with dosing cup provided. Dosing cup to be used with this product only. Do not use with other products.
- mL= milliliter

1. Age

1. dose

1. adults and children 12 years of age and over

1. 15 mL or 30 mL

1. children 2 to under 12 years of age

1. 5 ml or 10 mL

Other information

- store at room temperature away from heat and direct light; keep from freezing
- do not use if printed seal under cap is broken or missing

Inactive ingredients

FD&C Red No. 40, flavors, glycerin, methylparaben, purified water.

Questions or Comments?

1-800-632-6900

NDC 30142-708-04

COMPARE TO the active ingredients EMETROL®* See back panel

Kroger®

Nausea Relief

For Nausea Due to Upset Stomach

For Children & Adults

- No Antihistamines
- No Aspirin
- No Alcohol
- No caffeine

Naturally Cherry Flavor

Naturally and Artificially Flavored

4 FL OZ (118 mL)

IMPORTANT:KEEP THIS CARTON FOR FUTURE REFERENCE ON FULL LABELING.

*Emetrol®is a registered trademark of Wellspring Pharmaceuticals Corporation, Sarasota, FL 34243. Wellspring Pharmaceuticals Corporation is not affiliated with The Kroger Co. or this product.

DISTRIBUTED BY THE KROGER CO.

CINCINNATI, OHIO 45202

QUALITY GUARANTEE

800-632-6900

www.kroger.com